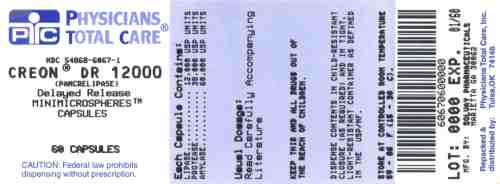 DRUG LABEL: Creon
NDC: 54868-6067 | Form: CAPSULE, DELAYED RELEASE PELLETS
Manufacturer: Physicians Total Care, Inc.
Category: prescription | Type: HUMAN PRESCRIPTION DRUG LABEL
Date: 20120206

ACTIVE INGREDIENTS: PANCRELIPASE LIPASE 12000 [USP'U]/1 1; PANCRELIPASE PROTEASE 38000 [USP'U]/1 1; PANCRELIPASE AMYLASE 60000 [USP'U]/1 1
INACTIVE INGREDIENTS: cetyl alcohol; dimethicone; polyethylene glycol; triethyl citrate; hypromelloses

HIGHLIGHTS OF PRESCRIBING INFORMATION

These highlights do not include all the information needed to use CREON safely and effectively. See full prescribing information for CREON.
CREON (pancrelipase) delayed-release capsules for oral use
Initial U.S. Approval: 2009

RECENT MAJOR CHANGES

Dosage and Administration, Infants (up to 12 months) (2.1) 6/2011

Dosage and Administration (2.2) 6/2011

Dosage and Administration, Infants (up to 12 months) (2.2) 6/2011

1 INDICATIONS AND USAGE

CREON is a combination of porcine-derived lipases, proteases, and amylases indicated for the treatment of exocrine pancreatic insufficiency due to cystic fibrosis, chronic pancreatitis, pancreatectomy, or other conditions. (1)

2 DOSAGE AND ADMINISTRATION

CREON is not interchangeable with any other pancrelipase product. (2.1)

Do not crush or chew capsules and capsule contents. For infants or patients unable to swallow intact capsules, the contents may be sprinkled on soft acidic food, e.g., applesauce. (2.1) Dosing should not exceed the recommended maximum dosage set forth by the Cystic Fibrosis Foundation Consensus Conferences Guidelines. (2.2)

Infants (up to 12 months)

- Prior to each feeding, infants may be given 3,000 lipase units (one capsule) per 120 mL of formula or per breast-feeding. (2.1)
- Do not mix CREON capsule contents directly into formula or breast milk prior to administration. (2.1)

Children Older than 12 Months and Younger than 4 Years

- Begin with 1,000 lipase units/kg of body weight per meal for children less than age 4 years to a maximum of 2,500 lipase units/kg of body weight per meal (or less than or equal to 10,000 lipase units/kg of body weight per day), or less than 4,000 lipase units/g fat ingested per day. (2.2)

Children 4 Years and Older and Adults

- Begin with 500 lipase units/kg of body weight per meal for those older than age 4 years to a maximum of 2,500 lipase units/kg of body weight per meal (or less than or equal to 10,000 lipase units/kg of body weight per day), or less than 4,000 lipase units/g fat ingested per day. (2.2)

Adults with Exocrine Pancreatic Insufficiency Due to Chronic Pancreatitis or Pancreatectomy

- Individualize dosage based on clinical symptoms, the degree of steatorrhea present and the fat content of the diet. (2.2)

3 DOSAGE FORMS AND STRENGTHS

- Delayed-Release Capsules: 3,000 USP units of lipase; 9,500 USP units of protease; 15,000 USP units of amylase (3)
- Delayed-Release Capsules: 6,000 USP units of lipase; 19,000 USP units of protease; 30,000 USP units of amylase (3)
- Delayed-Release Capsules: 12,000 USP units of lipase; 38,000 USP units of protease; 60,000 USP units of amylase (3)
- Delayed-Release Capsules: 24,000 USP units of lipase; 76,000 USP units of protease; 120,000 USP units of amylase (3)

4 CONTRAINDICATIONS

None (4)

5 WARNINGS AND PRECAUTIONS

- Fibrosing colonopathy is associated with high-dose use of pancreatic enzyme replacement in the treatment of cystic fibrosis patients. Exercise caution when doses of CREON exceed 2,500 lipase units/kg of body weight per meal (or greater than 10,000 lipase units/kg of body weight per day). (5.1)
- To avoid irritation of oral mucosa, do not chew CREON or retain in the mouth. (5.2)
- Exercise caution when prescribing CREON to patients with gout, renal impairment, or hyperuricemia. (5.3)
- There is theoretical risk of viral transmission with all pancreatic enzyme products including CREON. (5.4)
- Exercise caution when administering pancrelipase to a patient with a known allergy to proteins of porcine origin. (5.5)

6 ADVERSE REACTIONS

- Adverse reactions occurring in at least 2 cystic fibrosis patients (greater than or equal to 4%) receiving CREON are vomiting, dizziness, and cough. (6.1)
- Adverse reactions that occurred in at least 1 chronic pancreatitis or pancreatectomy patient (greater than or equal to 4%) receiving CREON are hyperglycemia, hypoglycemia, abdominal pain, abnormal feces, flatulence, frequent bowel movements, and nasopharyngitis. (6.1)

To report SUSPECTED ADVERSE REACTIONS, contact Abbott Laboratories at 1-800-241-1643 or FDA at 1-800-FDA-1088 or www.fda.gov/medwatch.

FULL PRESCRIBING INFORMATION

1 INDICATIONS AND USAGE

CREON® (pancrelipase) is indicated for the treatment of exocrine pancreatic insufficiency due to cystic fibrosis, chronic pancreatitis, pancreatectomy, or other conditions.

2 DOSAGE AND ADMINISTRATION

CREON is not interchangeable with other pancrelipase products.

CREON is orally administered. Therapy should be initiated at the lowest recommended dose and gradually increased. The dosage of CREON should be individualized based on clinical symptoms, the degree of steatorrhea present, and the fat content of the diet as described in the Limitations on Dosing below [see Dosage and Administration (2.2) and Warnings and Precautions (5.1)].

2.1 Administration

Infants (up to 12 months)

CREON should be administered to infants immediately prior to each feeding, using a dosage of 3,000 lipase units per 120 mL of formula or prior to breast-feeding. Contents of the capsule may be administered directly to the mouth or with a small amount of applesauce. Administration should be followed by breast milk or formula. Contents of the capsule should not be mixed directly into formula or breast milk as this may diminish efficacy. Care should be taken to ensure that CREON is not crushed or chewed or retained in the mouth, to avoid irritation of the oral mucosa.

Children and Adults

CREON should be taken during meals or snacks, with sufficient fluid. CREON capsules and capsule contents should not be crushed or chewed. Capsules should be swallowed whole.

For patients who are unable to swallow intact capsules, the capsules may be carefully opened and the contents added to a small amount of acidic soft food with a pH of 4.5 or less, such as applesauce, at room temperature. The CREON-soft food mixture should be swallowed immediately without crushing or chewing, and followed with water or juice to ensure complete ingestion. Care should be taken to ensure that no drug is retained in the mouth.

2.2 Dosage

Dosage recommendations for pancreatic enzyme replacement therapy were published following the Cystic Fibrosis Foundation Consensus Conferences.^(1, 2, 3) CREON should be administered in a manner consistent with the recommendations of the Cystic Fibrosis Foundation Consensus Conferences (also known as Conferences) provided in the following paragraphs, except for infants. Although the Conferences recommend doses of 2,000 to 4,000 lipase units in infants up to 12 months, CREON is available in a 3,000 lipase unit capsule. Therefore, the recommended dose of CREON in infants up to 12 months is 3,000 lipase units per 120 mL of formula or per breast-feeding. Patients may be dosed on a fat ingestion-based or actual body weight-based dosing scheme.

Additional recommendations for pancreatic enzyme therapy in patients with exocrine pancreatic insufficiency due to chronic pancreatitis or pancreatectomy are based on a clinical trial conducted in these populations.

Infants (up to 12 months)

CREON is available in the strength of 3,000 USP units of lipase thus infants may be given 3,000 lipase units (one capsule) per 120 mL of formula or per breast-feeding. Do not mix CREON capsule contents directly into formula or breast milk prior to administration [see Administration (2.1)].

Children Older than 12 Months and Younger than 4 Years

Enzyme dosing should begin with 1,000 lipase units/kg of body weight per meal for children less than age 4 years to a maximum of 2,500 lipase units/kg of body weight per meal (or less than or equal to 10,000 lipase units/kg of body weight per day), or less than 4,000 lipase units/g fat ingested per day.

Children 4 Years and Older and Adults

Enzyme dosing should begin with 500 lipase units/kg of body weight per meal for those older than age 4 years to a maximum of 2,500 lipase units/kg of body weight per meal (or less than or equal to 10,000 lipase units/kg of body weight per day), or less than 4,000 lipase units/g fat ingested per day.

Usually, half of the prescribed CREON dose for an individualized full meal should be given with each snack. The total daily dose should reflect approximately three meals plus two or three snacks per day.

Enzyme doses expressed as lipase units/kg of body weight per meal should be decreased in older patients because they weigh more but tend to ingest less fat per kilogram of body weight.

Adults with Exocrine Pancreatic Insufficiency Due to Chronic Pancreatitis or Pancreatectomy

The initial starting dose and increases in the dose per meal should be individualized based on clinical symptoms, the degree of steatorrhea present, and the fat content of the diet.

In one clinical trial, patients received CREON at a dose of 72,000 lipase units per meal while consuming at least 100 g of fat per day [see Clinical Studies (14.2)]. Lower starting doses recommended in the literature are consistent with the 500 lipase units/kg of body weight per meal lowest starting dose recommended for adults in the Cystic Fibrosis Foundation Consensus Conferences Guidelines.^(1, 2, 3, 4) Usually, half of the prescribed CREON dose for an individualized full meal should be given with each snack.

Limitations on Dosing

Dosing should not exceed the recommended maximum dosage set forth by the Cystic Fibrosis Foundation Consensus Conferences Guidelines.^(1, 2, 3) If symptoms and signs of steatorrhea persist, the dosage may be increased by the healthcare professional. Patients should be instructed not to increase the dosage on their own. There is great inter-individual variation in response to enzymes; thus, a range of doses is recommended. Changes in dosage may require an adjustment period of several days. If doses are to exceed 2,500 lipase units/kg of body weight per meal, further investigation is warranted. Doses greater than 2,500 lipase units/kg of body weight per meal (or greater than 10,000 lipase units/kg of body weight per day) should be used with caution and only if they are documented to be effective by 3-day fecal fat measures that indicate a significantly improved coefficient of fat absorption. Doses greater than 6,000 lipase units/kg of body weight per meal have been associated with colonic stricture, indicative of fibrosing colonopathy, in children less than 12 years of age [see Warnings and Precautions (5.1)]. Patients currently receiving higher doses than 6,000 lipase units/kg of body weight per meal should be examined and the dosage either immediately decreased or titrated downward to a lower range.

3 DOSAGE FORMS AND STRENGTHS

The active ingredient in CREON evaluated in clinical trials is lipase. CREON is dosed by lipase units.

Other active ingredients include protease and amylase. Each CREON delayed-release capsule strength contains the specified amounts of lipase, protease, and amylase as follows:

- 3,000 USP units of lipase; 9,500 USP units of protease; 15,000 USP units of amylase delayed-release capsules have a white opaque cap with imprint “CREON 1203” and a white opaque body.
- 6,000 USP units of lipase; 19,000 USP units of protease; 30,000 USP units of amylase delayed-release capsules have an orange opaque cap with imprint “CREON 1206” and a blue opaque body.
- 12,000 USP units of lipase; 38,000 USP units of protease; 60,000 USP units of amylase delayed-release capsules have a brown opaque cap with imprint “CREON 1212” and a colorless transparent body.
- 24,000 USP units of lipase; 76,000 USP units of protease; 120,000 USP units of amylase delayed-release capsules have an orange opaque cap with imprint “CREON 1224” and a colorless transparent body.

4 CONTRAINDICATIONS

None.

5 WARNINGS AND PRECAUTIONS

5.1 Fibrosing Colonopathy

Fibrosing colonopathy has been reported following treatment with different pancreatic enzyme products. ^(5, 6) Fibrosing colonopathy is a rare, serious adverse reaction initially described in association with high-dose pancreatic enzyme use, usually over a prolonged period of time and most commonly reported in pediatric patients with cystic fibrosis. The underlying mechanism of fibrosing colonopathy remains unknown. Doses of pancreatic enzyme products exceeding 6,000 lipase units/kg of body weight per meal have been associated with colonic stricture in children less than 12 years of age.^1 Patients with fibrosing colonopathy should be closely monitored because some patients may be at risk of progressing to stricture formation. It is uncertain whether regression of fibrosing colonopathy occurs.^1 It is generally recommended, unless clinically indicated, that enzyme doses should be less than 2,500 lipase units/kg of body weight per meal (or less than 10,000 lipase units/kg of body weight per day) or less than 4,000 lipase units/g fat ingested per day [see Dosage and Administration (2.1)].

Doses greater than 2,500 lipase units/kg of body weight per meal (or greater than 10,000 lipase units/kg of body weight per day) should be used with caution and only if they are documented to be effective by 3-day fecal fat measures that indicate a significantly improved coefficient of fat absorption. Patients receiving higher doses than 6,000 lipase units/kg of body weight per meal should be examined and the dosage either immediately decreased or titrated downward to a lower range.

5.2 Potential for Irritation to Oral Mucosa

Care should be taken to ensure that no drug is retained in the mouth. CREON should not be crushed or chewed or mixed in foods having a pH greater than 4.5. These actions can disrupt the protective enteric coating resulting in early release of enzymes, irritation of oral mucosa, and/or loss of enzyme activity [see Dosage and Administration (2.2) and Patient Counseling Information (17.1)]. For patients who are unable to swallow intact capsules, the capsules may be carefully opened and the contents added to a small amount of acidic soft food with a pH of 4.5 or less, such as applesauce, at room temperature. The CREON-soft food mixture should be swallowed immediately and followed with water or juice to ensure complete ingestion.

5.3 Potential for Risk of Hyperuricemia

Caution should be exercised when prescribing CREON to patients with gout, renal impairment, or hyperuricemia. Porcine-derived pancreatic enzyme products contain purines that may increase blood uric acid levels.

5.4 Potential Viral Exposure from the Product Source

CREON is sourced from pancreatic tissue from swine used for food consumption. Although the risk that CREON will transmit an infectious agent to humans has been reduced by testing for certain viruses during manufacturing and by inactivating certain viruses during manufacturing, there is a theoretical risk for transmission of viral disease, including diseases caused by novel or unidentified viruses. Thus, the presence of porcine viruses that might infect humans cannot be definitely excluded. However, no cases of transmission of an infectious illness associated with the use of porcine pancreatic extracts have been reported.

5.5 Allergic Reactions

Caution should be exercised when administering pancrelipase to a patient with a known allergy to proteins of porcine origin. Rarely, severe allergic reactions including anaphylaxis, asthma, hives, and pruritus, have been reported with other pancreatic enzyme products with different formulations of the same active ingredient (pancrelipase). The risks and benefits of continued CREON treatment in patients with severe allergy should be taken into consideration with the overall clinical needs of the patient.

6 ADVERSE REACTIONS

The most serious adverse reactions reported with different pancreatic enzyme products of the same active ingredient (pancrelipase) that are described elsewhere in the label include fibrosing colonopathy, hyperuricemia and allergic reactions [see Warnings and Precautions (5)].

6.1 Clinical Trials Experience

Because clinical trials are conducted under widely varying conditions, adverse reaction rates observed in the clinical trials of a drug cannot be directly compared to the rates in the clinical trials of another drug and may not reflect the rates observed in practice.

The short-term safety of CREON was assessed in clinical trials conducted in 121 patients with exocrine pancreatic insufficiency (EPI): 67 patients with EPI due to cystic fibrosis (CF) and 25 patients with EPI due to chronic pancreatitis or pancreatectomy were treated with CREON.

Cystic Fibrosis

Studies 1 and 2 were randomized, double-blind, placebo-controlled, crossover studies of 49 patients, ages 7 to 43 years, with EPI due to CF. Study 1 included 32 patients ages 12 to 43 years and Study 2 included 17 patients ages 7 to 11 years. In these studies, patients were randomized to receive CREON at a dose of 4,000 lipase units/g fat ingested per day or matching placebo for 5 to 6 days of treatment, followed by crossover to the alternate treatment for an additional 5 to 6 days. The mean exposure to CREON during these studies was 5 days.

In Study 1, one patient experienced duodenitis and gastritis of moderate severity 16 days after completing treatment with CREON. Transient neutropenia without clinical sequelae was observed as an abnormal laboratory finding in one patient receiving CREON and a macrolide antibiotic.

In Study 2, adverse reactions that occurred in at least 2 patients (greater than or equal to 12%) treated with CREON were vomiting and headache. Vomiting occurred in 2 patients treated with CREON and did not occur in patients treated with placebo; headache occurred in 2 patients treated with CREON and did not occur in patients treated with placebo.

The most common adverse reactions (greater than or equal to 4%) in Studies 1 and 2 were vomiting, dizziness, and cough. Table 1 enumerates adverse reactions that occurred in at least 2 patients (greater than or equal to 4%) treated with CREON at a higher rate than with placebo in Studies 1 and 2.

Table 1: Adverse Reactions Occurring in at Least 2 Patients (greater than or equal to 4%) in Cystic Fibrosis (Studies 1 and 2)
Adverse Reaction | CREON Capsules n = 49 (%) | Placebo n = 47 (%)
Vomiting | 3 (6) | 1 (2)
Dizziness | 2 (4) | 1 (2)
Cough | 2 (4) | 0

An additional open-label, single-arm study assessed the short-term safety and tolerability of CREON in 18 infants and children, ages 4 months to 6 years, with EPI due to cystic fibrosis. Patients received their usual pancreatic enzyme replacement therapy (mean dose of 7,000 lipase units/kg/day for a mean duration of 18.2 days) followed by CREON (mean dose of 7,500 lipase units/kg/day for a mean duration of 12.6 days). There were no serious adverse reactions. Adverse reactions that occurred in patients during treatment with CREON were vomiting, irritability, and decreased appetite, each occurring in 6% of patients.

Chronic Pancreatitis or Pancreatectomy

A randomized, double-blind, placebo-controlled, parallel group study was conducted in 54 adult patients, ages 32 to 75 years, with EPI due to chronic pancreatitis or pancreatectomy. Patients received single-blind placebo treatment during a 5-day run-in period followed by an intervening period of up to 16 days of investigator-directed treatment with no restrictions on pancreatic enzyme replacement therapy. Patients were then randomized to receive CREON or matching placebo for 7 days. The CREON dose was 72,000 lipase units per main meal (3 main meals) and 36,000 lipase units per snack (2 snacks). The mean exposure to CREON during this study was 6.8 days in the 25 patients that received CREON.

The most common adverse reactions reported during the study were related to glycemic control and were reported more commonly during CREON treatment than during placebo treatment.

Table 2 enumerates adverse reactions that occurred in at least 1 patient (greater than or equal to 4%) treated with CREON at a higher rate than with placebo.

Table 2: Adverse Reactions in at Least 1 Patient (greater than or equal to 4%) in the Chronic Pancreatitis or Pancreatectomy Trial
Adverse Reaction | CREON Capsules n = 25 (%) | Placebo n = 29 (%)
Hyperglycemia | 2 (8) | 2 (7)
Hypoglycemia | 1 (4) | 1 (3)
Abdominal Pain | 1 (4) | 1 (3)
Abnormal Feces | 1 (4) | 0
Flatulence | 1 (4) | 0
Frequent Bowel Movements | 1 (4) | 0
Nasopharyngitis | 1 (4) | 0

6.2 Postmarketing Experience

Postmarketing data from this formulation of CREON have been available since 2009. The following adverse reactions have been identified during post approval use of this formulation of CREON. Because these reactions are reported voluntarily from a population of uncertain size, it is not always possible to reliably estimate their frequency or establish a causal relationship to drug exposure.

Gastrointestinal disorders (including abdominal pain, diarrhea, flatulence, constipation and nausea), skin disorders (including pruritus, urticaria and rash), blurred vision, myalgia, muscle spasm, and asymptomatic elevations of liver enzymes have been reported with this formulation of CREON.

Delayed- and immediate-release pancreatic enzyme products with different formulations of the same active ingredient (pancrelipase) have been used for the treatment of patients with exocrine pancreatic insufficiency due to cystic fibrosis and other conditions, such as chronic pancreatitis. The long-term safety profile of these products has been described in the medical literature. The most serious adverse reactions included fibrosing colonopathy, distal intestinal obstruction syndrome (DIOS), recurrence of pre-existing carcinoma, and severe allergic reactions including anaphylaxis, asthma, hives, and pruritus.

7 DRUG INTERACTIONS

No drug interactions have been identified. No formal interaction studies have been conducted.

8 USE IN SPECIFIC POPULATIONS

8.1 Pregnancy

Teratogenic effects

Pregnancy Category C: Animal reproduction studies have not been conducted with pancrelipase. It is also not known whether pancrelipase can cause fetal harm when administered to a pregnant woman or can affect reproduction capacity. CREON should be given to a pregnant woman only if clearly needed. The risk and benefit of pancrelipase should be considered in the context of the need to provide adequate nutritional support to a pregnant woman with exocrine pancreatic insufficiency. Adequate caloric intake during pregnancy is important for normal maternal weight gain and fetal growth. Reduced maternal weight gain and malnutrition can be associated with adverse pregnancy outcomes.

8.3 Nursing Mothers

It is not known whether this drug is excreted in human milk. Because many drugs are excreted in human milk, caution should be exercised when CREON is administered to a nursing woman. The risk and benefit of pancrelipase should be considered in the context of the need to provide adequate nutritional support to a nursing mother with exocrine pancreatic insufficiency.

8.4 Pediatric Use

The short-term safety and effectiveness of CREON were assessed in two randomized, double-blind, placebo-controlled, crossover studies of 49 patients with EPI due to cystic fibrosis, 25 of whom were pediatric patients. Study 1 included 8 adolescents between 12 and 17 years of age. Study 2 included 17 children between 7 and 11 years of age. The safety and efficacy in pediatric patients in these studies were similar to adult patients [see Adverse Reactions (6.1) and Clinical Studies (14)].

An open-label, single-arm, short-term study of CREON was conducted in 18 infants and children, ages 4 months to six years of age, with EPI due to cystic fibrosis. Patients received their usual pancreatic enzyme replacement therapy (mean dose of 7,000 lipase units/kg/day for a mean duration of 18.2 days) followed by CREON (mean dose of 7,500 lipase units/kg/day for a mean duration of 12.6 days). The mean daily fat intake was 48 grams during treatment with usual pancreatic enzyme replacement therapy and 47 grams during treatment with CREON. When patients were switched from their usual pancreatic enzyme replacement therapy to CREON, they demonstrated similar spot fecal fat testing results; the clinical relevance of spot fecal fat testing has not been demonstrated. Adverse reactions that occurred in patients during treatment with CREON were vomiting, irritability, and decreased appetite [see Adverse Reactions (6.1)].

The safety and efficacy of pancreatic enzyme products with different formulations of pancrelipase consisting of the same active ingredient (lipases, proteases, and amylases) for treatment of children with exocrine pancreatic insufficiency due to cystic fibrosis have been described in the medical literature and through clinical experience.

Dosing of pediatric patients should be in accordance with recommended guidance from the Cystic Fibrosis Foundation Consensus Conferences [see Dosage and Administration (2.1)]. Doses of other pancreatic enzyme products exceeding 6,000 lipase units/kg of body weight per meal have been associated with fibrosing colonopathy and colonic strictures in children less than 12 years of age [see Warnings and Precautions (5.1)].

8.5 Geriatric Use

Clinical studies of CREON did not include sufficient numbers of subjects aged 65 and over to determine whether they respond differently from younger subjects. Other reported clinical experience has not identified differences in responses between the elderly and younger patients.

10 OVERDOSAGE

There have been no reports of overdose in clinical trials or postmarketing surveillance with this formulation of CREON. Chronic high doses of pancreatic enzyme products have been associated with fibrosing colonopathy and colonic strictures [see Dosage and Administration (2.2) and Warnings and Precautions (5.1)]. High doses of pancreatic enzyme products have been associated with hyperuricosuria and hyperuricemia, and should be used with caution in patients with a history of hyperuricemia, gout, or renal impairment [see Warnings and Precautions (5.3)].

11 DESCRIPTION

CREON is a pancreatic enzyme preparation consisting of pancrelipase, an extract derived from porcine pancreatic glands. Pancrelipase contains multiple enzyme classes, including porcine-derived lipases, proteases, and amylases.

Pancrelipase is a beige-white amorphous powder. It is miscible in water and practically insoluble or insoluble in alcohol and ether.

Each delayed-release capsule for oral administration contains enteric-coated spheres (0.71–1.60 mm in diameter).

The active ingredient evaluated in clinical trials is lipase. CREON is dosed by lipase units.

Other active ingredients include protease and amylase.

CREON contains the following inactive ingredients: cetyl alcohol, dimethicone, hypromellose phthalate, polyethylene glycol, and triethyl citrate.

3,000 USP units of lipase; 9,500 USP units of protease; 15,000 USP units of amylase delayed-release capsules have a white opaque cap with imprint “CREON 1203” and a white opaque body. The shells contain titanium dioxide and hypromellose.

6,000 USP units of lipase; 19,000 USP units of protease; 30,000 USP units of amylase delayed-release capsules have a Swedish-orange opaque cap with imprint “CREON 1206” and a blue opaque body. The shells contain FD&C Blue No. 2, gelatin, red iron oxide, sodium lauryl sulfate, titanium dioxide, and yellow iron oxide.

12,000 USP units of lipase; 38,000 USP units of protease; 60,000 USP units of amylase delayed-release capsules have a brown opaque cap with imprint “CREON 1212” and a colorless transparent body. The shells contain black iron oxide, gelatin, red iron oxide, sodium lauryl sulfate, titanium dioxide, and yellow iron oxide.

24,000 USP units of lipase; 76,000 USP units of protease; 120,000 USP units of amylase delayed-release capsules have a Swedish-orange opaque cap with imprint “CREON 1224” and a colorless transparent body. The shells contain gelatin, red iron oxide, sodium lauryl sulfate, titanium dioxide, and yellow iron oxide.

12 CLINICAL PHARMACOLOGY

12.1 Mechanism of Action

The pancreatic enzymes in CREON catalyze the hydrolysis of fats to monoglyceride, glycerol and free fatty acids, proteins into peptides and amino acids, and starches into dextrins and short chain sugars such as maltose and maltriose in the duodenum and proximal small intestine, thereby acting like digestive enzymes physiologically secreted by the pancreas.

12.3 Pharmacokinetics

The pancreatic enzymes in CREON are enteric-coated to minimize destruction or inactivation in gastric acid. CREON is designed to release most of the enzymes in vivo at an approximate pH of 5.5 or greater. Pancreatic enzymes are not absorbed from the gastrointestinal tract in appreciable amounts.

13 NONCLINICAL TOXICOLOGY

13.1 Carcinogenesis, Mutagenesis, Impairment of Fertility

Carcinogenicity, genetic toxicology, and animal fertility studies have not been performed with pancrelipase.

14 CLINICAL STUDIES

The short-term efficacy of CREON was evaluated in three studies conducted in 103 patients with exocrine pancreatic insufficiency (EPI). Two studies were conducted in 49 patients with EPI due to cystic fibrosis (CF); one study was conducted in 54 patients with EPI due to chronic pancreatitis or pancreatectomy.

14.1 Cystic Fibrosis

Studies 1 and 2 were randomized, double-blind, placebo-controlled, crossover studies in 49 patients, ages 7 to 43 years, with exocrine pancreatic insufficiency due to cystic fibrosis. Study 1 included patients aged 12 to 43 years (n = 32). The final analysis population was limited to 29 patients; 3 patients were excluded due to protocol deviations. Study 2 included patients aged 7 to 11 years (n = 17). The final analysis population was limited to 16 patients; 1 patient withdrew consent prior to stool collection during treatment with CREON. In each study, patients were randomized to receive CREON at a dose of 4,000 lipase units/g fat ingested per day or matching placebo for 5 to 6 days of treatment, followed by crossover to the alternate treatment for an additional 5 to 6 days. All patients consumed a high-fat diet (greater than or equal to 90 grams of fat per day, 40% of daily calories derived from fat) during the treatment periods.

The coefficient of fat absorption (CFA) was determined by a 72-hour stool collection during both treatments, when both fat excretion and fat ingestion were measured. Each patient's CFA during placebo treatment was used as their no-treatment CFA value.

In Study 1, mean CFA was 89% with CREON treatment compared to 49% with placebo treatment. The mean difference in CFA was 41 percentage points in favor of CREON treatment with 95% CI: (34, 47) and p<0.001.

In Study 2, mean CFA was 83% with CREON treatment compared to 47% with placebo treatment. The mean difference in CFA was 35 percentage points in favor of CREON treatment with 95% CI: (27, 44) and p<0.001.

Subgroup analyses of the CFA results in Studies 1 and 2 showed that mean change in CFA with CREON treatment was greater in patients with lower no-treatment (placebo) CFA values than in patients with higher no-treatment (placebo) CFA values. There were no differences in response to CREON by age or gender, with similar responses to CREON observed in male and female patients, and in younger (under 18 years of age) and older patients.

The coefficient of nitrogen absorption (CNA) was determined by a 72-hour stool collection during both treatments, when nitrogen excretion was measured and nitrogen ingestion from a controlled diet was estimated (based on the assumption that proteins contain 16% nitrogen). Each patient's CNA during placebo treatment was used as their no-treatment CNA value.

In Study 1, mean CNA was 86% with CREON treatment compared to 49% with placebo treatment. The mean difference in CNA was 37 percentage points in favor of CREON treatment with 95% CI: (31, 42) and p<0.001.

In Study 2, mean CNA was 80% with CREON treatment compared to 45% with placebo treatment. The mean difference in CNA was 35 percentage points in favor of CREON treatment with 95% CI: (26, 45) and p<0.001.

14.2 Chronic Pancreatitis or Pancreatectomy

A randomized, double-blind, placebo-controlled, parallel group study was conducted in 54 adult patients, ages 32 to 75 years, with EPI due to chronic pancreatitis or pancreatectomy. The final analysis population was limited to 52 patients; 2 patients were excluded due to protocol violations. Ten patients had a history of pancreatectomy (7 were treated with CREON). In this study, patients received placebo for 5 days (run-in period), followed by pancreatic enzyme replacement therapy as directed by the investigator for 16 days; this was followed by randomization to CREON or matching placebo for 7 days of treatment (double-blind period). Only patients with CFA less than 80% in the run-in period were randomized to the double-blind period. The dose of CREON during the double-blind period was 72,000 lipase units per main meal (3 main meals) and 36,000 lipase units per snack (2 snacks). All patients consumed a high-fat diet (greater than or equal to 100 grams of fat per day) during the treatment period.

The CFA was determined by a 72-hour stool collection during the run-in and double-blind treatment periods, when both fat excretion and fat ingestion were measured. The mean change in CFA from the run-in period to the end of the double-blind period in the CREON and Placebo groups is shown in Table 3.

Table 3: Change in CFA in the Chronic Pancreatitis and Pancreatectomy Trial (Run-in Period to End of Double-Blind Period)
 | CREON n = 24 | Placebo n = 28
CFA [%]
Run-in Period (Mean, SD) | 54 (19) | 57 (21)
End of Double-Blind Period (Mean, SD) | 86 (6) | 66 (20)
Change in CFA * [%]
Run-in Period to End of Double-Blind Period (Mean, SD) | 32 (18) | 9 (13)
Treatment Difference (95% CI) | 21 (14, 28)
*p<0.0001

Subgroup analyses of the CFA results showed that mean change in CFA was greater in patients with lower run-in period CFA values than in patients with higher run-in period CFA values. Only 1 of the patients with a history of total pancreatectomy was treated with CREON in the study. That patient had a CFA of 26% during the run-in period and a CFA of 73% at the end of the double-blind period. The remaining 6 patients with a history of partial pancreatectomy treated with CREON on the study had a mean CFA of 42% during the run-in period and a mean CFA of 84% at the end of the double-blind period.

15 REFERENCES

^1 Borowitz DS, Grand RJ, Durie PR, et al. Use of pancreatic enzyme supplements for patients with cystic fibrosis in the context of fibrosing colonopathy. Journal of Pediatrics. 1995; 127: 681-684.

^2 Borowitz DS, Baker RD, Stallings V. Consensus report on nutrition for pediatric patients with cystic fibrosis. Journal of Pediatric Gastroenterology Nutrition. 2002 Sep; 35: 246-259.

^3 Stallings VA, Stark LJ, Robinson KA, et al. Evidence-based practice recommendations for nutrition-related management of children and adults with cystic fibrosis and pancreatic insufficiency: results of a systematic review. Journal of the American Dietetic Association. 2008; 108: 832-839.

^4 Dominguez-Munoz JE. Pancreatic enzyme therapy for pancreatic exocrine insufficiency. Current Gastroenterology Reports. 2007; 9: 116-122.

^5 Smyth RL, Ashby D, O'Hea U, et al. Fibrosing colonopathy in cystic fibrosis: results of a case-control study. Lancet. 1995; 346: 1247-1251.

^6 FitzSimmons SC, Burkhart GA, Borowitz DS, et al. High-dose pancreatic-enzyme supplements and fibrosing colonopathy in children with cystic fibrosis. New England Journal of Medicine. 1997; 336: 1283-1289.

16 HOW SUPPLIED/STORAGE AND HANDLING

CREON (pancrelipase) Delayed-Release Capsules

12,000 USP units of lipase; 38,000 USP units of protease; 60,000 USP units of amylase

Each CREON capsule is available as a two-piece gelatin capsule with a brown opaque cap with imprint “CREON 1212” and a colorless transparent body that contains tan-colored, delayed-release pancrelipase supplied in bottles of:

Bottles of 10 | NDC 54868-6067-0
Bottles of 60 | NDC 54868-6067-1

Storage and Handling

CREON must be stored at room temperature up to 25°C (77°F) and protected from moisture. Temperature excursions are permitted between 25°C to 40°C (77°F and 104°F) for up to 30 days. Product should be discarded if exposed to higher temperature and moisture conditions higher than 70%. After opening, keep bottle tightly closed between uses to protect from moisture.

Bottles of CREON 3,000 USP units of lipase must be stored and dispensed in the original container.

Do not crush CREON delayed-release capsules or the capsule contents.

17 PATIENT COUNSELING INFORMATION

See FDA-approved patient labeling (Medication Guide)

17.1 Dosing and Administration

- Instruct patients and caregivers that CREON should only be taken as directed by their healthcare professional. Patients should be advised that the total daily dose should not exceed 10,000 lipase units/kg body weight/day unless clinically indicated. This needs to be especially emphasized for patients eating multiple snacks and meals per day. Patients should be informed that if a dose is missed, the next dose should be taken with the next meal or snack as directed. Doses should not be doubled [see Dosage and Administration (2)].
- Instruct patients and caregivers that CREON should always be taken with food. Patients should be advised that CREON delayed-release capsules and the capsule contents must not be crushed or chewed as doing so could cause early release of enzymes and/or loss of enzymatic activity. Patients should swallow the intact capsules with adequate amounts of liquid at mealtimes. If necessary, the capsule contents can also be sprinkled on soft acidic foods [see Dosage and Administration (2)].

17.2 Fibrosing Colonopathy

Advise patients and caregivers to follow dosing instructions carefully, as doses of pancreatic enzyme products exceeding 6,000 lipase units/kg of body weight per meal have been associated with colonic strictures in children below the age of 12 years [see Dosage and Administration (2)].

17.3 Allergic Reactions

Advise patients and caregivers to contact their healthcare professional immediately if allergic reactions to CREON develop [see Warnings and Precautions (5.5)].

17.4 Pregnancy and Breast Feeding

- Instruct patients to notify their healthcare professional if they are pregnant or are thinking of becoming pregnant during treatment with CREON [see Use in Specific Populations (8.1)].
- Instruct patients to notify their healthcare professional if they are breast feeding or are thinking of breast feeding during treatment with CREON [see Use in Specific Populations (8.3)].

Manufactured by:

- Abbott Products GmbH
- Hannover, Germany

Marketed By:

- Abbott Laboratories
- North Chicago, IL 60064, U.S.A.

1055216 12E Rev Jul 2011

© 2011 Abbott Laboratories

Relabeling and Repackaging by:
Physicians Total Care, Inc.
Tulsa, Oklahoma 74146

MEDICATION GUIDE

CREON® (krē ′ŏn)

(pancrelipase)

Delayed-Release Capsules

Read this Medication Guide before you start taking CREON and each time you get a refill. There may be new information. This information does not take the place of talking to your doctor about your medical condition or treatment.

What is the most important information I should know about CREON?

CREON may increase your chance of having a rare bowel disorder called fibrosing colonopathy. This condition is serious and may require surgery. The risk of having this condition may be reduced by following the dosing instructions that your doctor gave you. Call your doctor right away if you have any unusual or severe:

- stomach area (abdominal) pain
- bloating
- trouble passing stool (having bowel movements)
- nausea, vomiting, or diarrhea

Take CREON exactly as prescribed. Do not take more or less CREON than directed by your doctor.

What is CREON?

CREON is a prescription medicine used to treat people who cannot digest food normally because their pancreas does not make enough enzymes due to cystic fibrosis, swelling of the pancreas that lasts a long time (chronic pancreatitis), removal of some or all of the pancreas (pancreatectomy), or other conditions. CREON may help your body use fats, proteins, and sugars from food.

CREON contains a mixture of digestive enzymes including lipases, proteases, and amylases from pig pancreas.

What should I tell my doctor before taking CREON?

Before taking CREON, tell your doctor about all your medical conditions, including if you:

- are allergic to pork (pig) products
- have a history of intestinal blockage of your intestines, or scarring or thickening of your bowel wall (fibrosing colonopathy)
- have gout, kidney disease, or high blood uric acid (hyperuricemia)
- have trouble swallowing capsules
- have any other medical condition
- are pregnant or plan to become pregnant. It is not known if CREON will harm your unborn baby.
- are breast-feeding or plan to breast-feed. It is not known if CREON passes into your breast milk.

Tell your doctor about all the medicines you take, including prescription and nonprescription medicines, vitamins, and herbal supplements.

Know the medicines you take. Keep a list of them and show it to your doctor and pharmacist when you get a new medicine.

How should I take CREON?

- Take CREON exactly as your doctor tells you.
- You should not switch CREON with any other pancreatic enzyme product without first talking to your doctor.
- Do not take more capsules in a day than the number your doctor tells you to take (total daily dose).
- Always take CREON with a meal or snack and enough liquid to swallow CREON completely. If you eat a lot of meals or snacks in a day, be careful not to go over your total daily dose.
- Your doctor may change your dose based on the amount of fatty foods you eat or based on your weight.
- Do not crush or chew CREON capsules or its contents, and do not hold the capsule or capsule contents in your mouth. Crushing, chewing or holding the CREON capsules in your mouth may cause irritation in your mouth or change the way CREON works in your body.

Giving CREON to infants (children up to 12 months)

1. Give CREON right before each feeding of formula or breast milk.
2. Do not mix CREON capsule contents directly into formula or breast milk.
3. Open the capsules and sprinkle the contents directly into your infant's mouth or mix the contents in a small amount of room temperature acidic soft food such as applesauce. These foods should be the kind found in baby food jars that you buy at the store, or other food recommended by your doctor.
4. If you sprinkle the CREON on food, give the CREON and food mixture to your child right away. Do not store CREON that is mixed with food.
5. Give your child enough liquid to completely swallow the CREON contents or the CREON and food mixture.
6. Look in your child's mouth to make sure that all of the medicine has been swallowed.

Giving CREON to children and adults

1. Swallow CREON capsules whole and take them with enough liquid to swallow them right away.
2. If you have trouble swallowing capsules, open the capsules and sprinkle the contents on a small amount of room temperature acidic food such as applesauce. Ask your doctor about other foods you can mix with CREON.
3. If you sprinkle CREON on food, swallow it right after you mix it and drink enough water or juice to make sure the medicine is swallowed completely. Do not store CREON that is mixed with food.
4. If you forget to take CREON, call your doctor or wait until your next meal and take your usual number of capsules. Take your next dose at your usual time. Do not make up for missed doses.

What are the possible side effects of CREON?

CREON may cause serious side effects, including:

- See “ What is the most important information I should know about CREON? ”
- Irritation of the inside of your mouth. This can happen if CREON is not swallowed completely.
- Increase in blood uric acid levels. This may cause worsening of swollen, painful joints (gout) caused by an increase in your blood uric acid levels.
- Allergic reactions, including trouble with breathing, skin rashes, or swollen lips.

Call your doctor right away if you have any of these symptoms.

The most common side effects of CREON include:

- Blood sugar increase (hyperglycemia) or decrease (hypoglycemia)
- Pain in your stomach (abdominal area)
- Frequent or abnormal bowel movements
- Gas
- Vomiting
- Dizziness
- Sore throat and cough

Other Possible Side Effects:

CREON and other pancreatic enzyme products are made from the pancreas of pigs, the same pigs people eat as pork. These pigs may carry viruses. Although it has never been reported, it may be possible for a person to get a viral infection from taking pancreatic enzyme products that come from pigs.

Tell your doctor if you have any side effect that bothers you or that does not go away.

These are not all the side effects of CREON. For more information, ask your doctor or pharmacist.

Call your doctor for medical advice about side effects. You may report side effects to the FDA at 1-800-FDA-1088.

You may also report side effects to Abbott Laboratories at 1-800-241-1643.

How should I store CREON?

- Store CREON at room temperature below 77°F (25°C). Avoid heat.
- You may store CREON at a temperature between 77°F to 104°F (25°C to 40°C) for up to 30 days. Throw away any CREON stored at these temperatures for more than 30 days.
- Keep CREON in a dry place and in the original container.
- After opening the bottle, keep it closed tightly between uses to protect from moisture.

Keep CREON and all medicines out of the reach of children.

General information about CREON

Medicines are sometimes prescribed for purposes other than those listed in a Medication Guide. Do not use CREON for a condition for which it was not prescribed. Do not give CREON to other people to take, even if they have the same symptoms you have. It may harm them.

This Medication Guide summarizes the most important information about CREON. If you would like more information, talk to your doctor. You can ask your doctor or pharmacist for information about CREON that is written for healthcare professionals. For more information, go to www.creon-us.com or call toll-free [1-800-241-1643].

What are the ingredients in CREON?

Active Ingredient: lipase, protease, amylase

Inactive Ingredients: cetyl alcohol, dimethicone, hypromellose phthalate, polyethylene glycol, and triethyl citrate.

The shells of the CREON 6,000 USP units of lipase, 12,000 USP units of lipase, and 24,000 USP units of lipase strengths contain: gelatin, red iron oxide, sodium lauryl sulfate, titanium dioxide, and yellow iron oxide.

In addition:

The shells for the CREON 3,000 USP units of lipase contain titanium dioxide and hypromellose.

The shells of the 6,000 USP units of lipase strength capsules contain FD&C Blue No. 2.

The shells of the 12,000 USP units of lipase strength capsules contain black iron oxide.

This Medication Guide has been approved by the U.S. Food and Drug Administration.

Manufactured for:

Abbott Laboratories
North Chicago, IL 60064, U.S.A.

1055216 12E Rev Jul 2011

© 2011 Abbott Laboratories

Rev July/2011

PACKAGE LABEL

CREON® (pancrelipase) Delayed-Release Capsules

DOSE BY LIPASE UNITS: Lipase 12,000 USP Units, Protease 38,000 USP Units, Amylase 60,000 USP Units

Each capsule contains pancrelipase in enteric-coated spheres.

Dispense enclosed Medication Guide to each patient.

Rx only